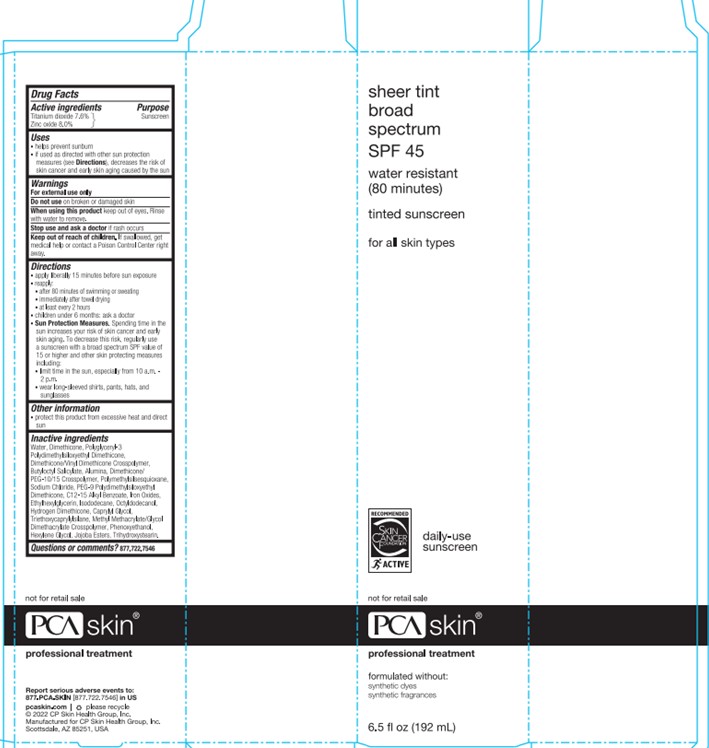 DRUG LABEL: sheer tint
NDC: 68726-269 | Form: LOTION
Manufacturer: CP Skin Health Group, Inc.
Category: otc | Type: HUMAN OTC DRUG LABEL
Date: 20240214

ACTIVE INGREDIENTS: ZINC OXIDE 8.1 g/100 mL; TITANIUM DIOXIDE 8 g/100 mL
INACTIVE INGREDIENTS: TRIETHOXYCAPRYLYLSILANE; WATER; DIMETHICONE; DIMETHICONE/PEG-10/15 CROSSPOLYMER; METHYL METHACRYLATE/GLYCOL DIMETHACRYLATE CROSSPOLYMER; ALKYL (C12-15) BENZOATE; BUTYLOCTYL SALICYLATE; SODIUM CHLORIDE; ETHYLHEXYLGLYCERIN; PHENOXYETHANOL; HEXYLENE GLYCOL; CAPRYLYL GLYCOL; HYDROGEN DIMETHICONE (13 CST); JOJOBA OIL, RANDOMIZED; TRIHYDROXYSTEARIN; ALUMINUM OXIDE; FERRIC OXIDE YELLOW; POLYGLYCERYL-3 POLYDIMETHYLSILOXYETHYL DIMETHICONE (4000 MPA.S); OCTYLDODECANOL; DIMETHICONE/VINYL DIMETHICONE CROSSPOLYMER (HARD PARTICLE); ISODODECANE; PEG-9 POLYDIMETHYLSILOXYETHYL DIMETHICONE; POLYMETHYLSILSESQUIOXANE (4.5 MICRONS); FERROSOFERRIC OXIDE; FERRIC OXIDE RED

PCA Skincare Sheer Tint Broad Spectrum SPF 45

Active Ingredients

Titanium Dioxide (7.6%)

Zinc Oxide (8.0%)

Purpose

Sunscreen

Uses

Helps prevent sunburn

if used as directed with other sun protection measures (see Directions), decreases the risk of skin cancer and early skin aging caused by the sun

Warnings

For external use only

Do not use on damaged or broken skin

Stop use and ask a doctor if skin rash occurs.

When using this product keep out of eyes. Rinse with water to remove

Keep out of reach of children. If product is swallowed, get medical help or contact a Poison Control Center right away.

Directions

Apply liberally 15 minutes before sun exposure

Reapply:

-after 80 minutes of swimming or sweating

-immediately after towel drying

-at least every 2 hours

Children under 6 montha: ask a doctor

Sun Protection Measures. Spending time in the sun increases your risk of skin cancer and early skin aging. To decrease this risk, regularly use a sunscreen with a broad spectrum SPF value of 15 or higher and other skin protecting measures including:

-limit time in the sun, especially from 10 a.m. - 2 p.m.

-wear long-sleeved shirts, pants, hats, and sunglasses.

Other Information

Protect this product from excessive heat and direct sun.

Questions?

Please call 877-722-7546

Inactive Ingredients

Alumina

Butyloctyl Salicylate

C12-15 Alkyl Benzoate

Caprylyl Glycol

Dimethicone

Dimethicone/PEG-10/15 Crosspolymer

Dimethicone/Vinyl Dimethicone Crosspolymer

Ethylhexylglycerin

Hexylene Glycol

Hydrogen Dimethicone

Iron Oxides

Isododecane

Jojoba Esters

Methyl Methacrylate/Glycol Dimethacrylate Crosspolymer

Octyldodecanol

PEG-9 Polydimethylsiloxyethyl Dimethicone

Phenoxyethanol

Polyglyceryl-3 Polydimethylsiloxyethyl Dimethicone

Polymethylsilsesquioxane

Sodium Chloride

Triethoxycaprylylsilane

Trihydroxystearin

Water